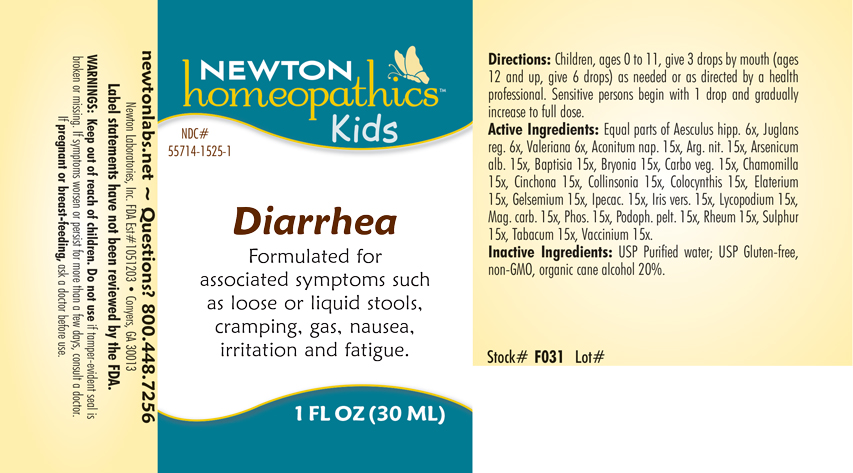 DRUG LABEL: Diarrhea
NDC: 55714-1525 | Form: LIQUID
Manufacturer: Newton Laboratories, Inc.
Category: homeopathic | Type: HUMAN OTC DRUG LABEL
Date: 20250127

ACTIVE INGREDIENTS: SILVER NITRATE 15 [hp_X]/1 mL; ARSENIC TRIOXIDE 15 [hp_X]/1 mL; BAPTISIA TINCTORIA ROOT 15 [hp_X]/1 mL; BRYONIA ALBA ROOT 15 [hp_X]/1 mL; ACTIVATED CHARCOAL 15 [hp_X]/1 mL; MATRICARIA CHAMOMILLA 15 [hp_X]/1 mL; CINCHONA OFFICINALIS BARK 15 [hp_X]/1 mL; COLLINSONIA CANADENSIS ROOT 15 [hp_X]/1 mL; GELSEMIUM SEMPERVIRENS ROOT 15 [hp_X]/1 mL; IPECAC 15 [hp_X]/1 mL; IRIS VERSICOLOR ROOT 15 [hp_X]/1 mL; LYCOPODIUM CLAVATUM SPORE 15 [hp_X]/1 mL; MAGNESIUM CARBONATE 15 [hp_X]/1 mL; PHOSPHORUS 15 [hp_X]/1 mL; PODOPHYLLUM 15 [hp_X]/1 mL; RHEUM OFFICINALE ROOT 15 [hp_X]/1 mL; SULFUR 15 [hp_X]/1 mL; TOBACCO LEAF 15 [hp_X]/1 mL; BILBERRY 15 [hp_X]/1 mL; ECBALLIUM ELATERIUM FRUIT 15 [hp_X]/1 mL; JUGLANS REGIA LEAF 6 [hp_X]/1 mL; HORSE CHESTNUT 6 [hp_X]/1 mL; CITRULLUS COLOCYNTHIS FRUIT PULP 15 [hp_X]/1 mL; VALERIAN 6 [hp_X]/1 mL; ACONITUM NAPELLUS 15 [hp_X]/1 mL
INACTIVE INGREDIENTS: WATER; ALCOHOL

Diarrhea 1525L

INDICATIONS AND USAGE SECTION

Formulated for associated symptoms such as loose or liquid stools, cramping, gas, nausea, irritation and fatigue.

DOSAGE & ADMINISTRATION SECTION

Directions: Children, ages 0 to 11, give 3 drops by mouth (ages 12 and up, give 6 drops) as needed or a directed by a health professional. Sensitive person begin with 1 drop and gradually increase to full dose.

OTC - ACTIVE INGREDIENT SECTION

Equal parts of Aesculus hippocastanum 6x, Juglans regia 6x, Valeriana officinalis 6x, Aconitum napellus 15x, Argentum nitricum 15x, Arsenicum album 15x, Baptisia tinctoria 15x, Bryonia 15x, Carbo vegetabilis 15x, Chamomilla 15x, Cinchona officinalis 15x, Collinsonia canadensis 15x, Colocynthis 15x, Elaterium 15x, Gelsemium sempervirens 15x, Ipecacuanha 15x, Iris versicolor 15x, Lycopodium clavatum 15x, Magnesia carbonica 15x, Phosphorus 15x, Podophyllum peltatum 15x, Rheum 15x, Sulphur 15x, Tabacum 15x, Vaccinium myrtillus 15x.

OTC - PURPOSE SECTION

Formulated for associated symptoms such as loose or liquid stools, cramping, gas, nausea, irritation and fatigue.

INACTIVE INGREDIENT SECTION

USP Purified water; USP Gluten-free, non-GMO, organic cane alcohol 20%

QUESTIONS SECTION

newtonlabs.net – Questions? 800.448.7256

Newton Laboratories, Inc. FDA Est # 1051203 - Conyers, GA 30013

WARNINGS SECTION

WARNINGS: Keep out of reach of children. Do not use if tamper-evident seal is broken or missing. If symptoms worsen or persist for more than a few days, consult a doctor. If pregnant or breast-feeding, ask a doctor before use.

OTC - PREGNANCY OR BREAST FEEDING SECTION

If pregnant or breast-feeding, ask a doctor before use.

OTC - KEEP OUT OF REACH OF CHILDREN SECTION

WARNINGS: Keep out of reach of children. Do not use if tamper-evident seal is broken or missing. If symptoms worsen or persist for more than a few days, consult a doctor. If pregnant or breast-feeding, ask a doctor before use.